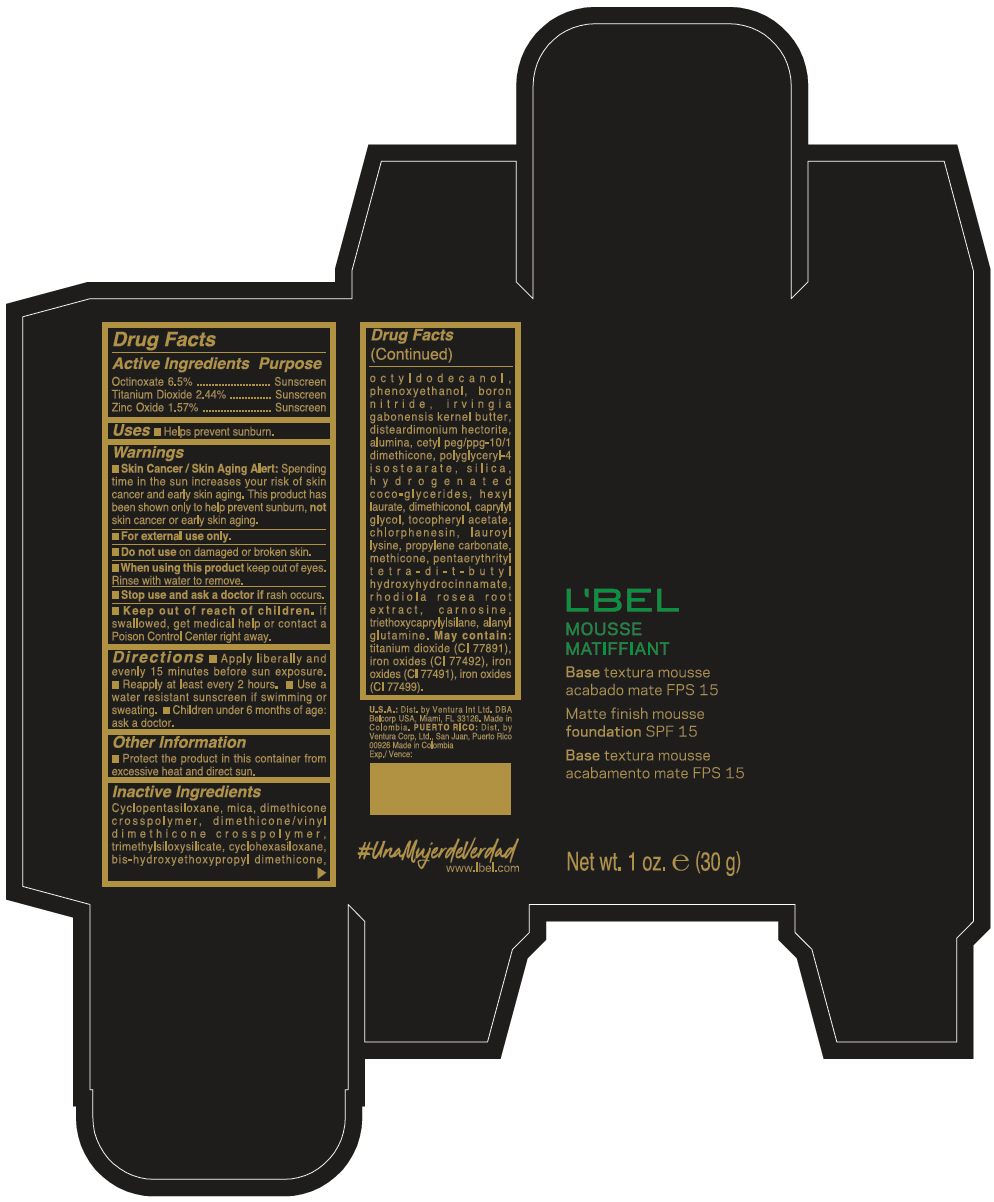 DRUG LABEL: LBEL MOUSSE MATIFFIANT MATTE FINISH MOUSSE FOUNDATION SPF 15 
NDC: 14141-079 | Form: PASTE
Manufacturer: Bel Star S.A. (Colombia)
Category: otc | Type: HUMAN OTC DRUG LABEL
Date: 20191115

ACTIVE INGREDIENTS: Octinoxate 0.065 g/1 g; Titanium Dioxide 0.0244 g/1 g; Zinc Oxide 0.0157 g/1 g
INACTIVE INGREDIENTS: CYCLOMETHICONE 5; MICA; DIMETHICONE CROSSPOLYMER (450000 MPA.S AT 12% IN CYCLOPENTASILOXANE); CYCLOMETHICONE 6; OCTYLDODECANOL; PHENOXYETHANOL; BORON NITRIDE; IRVINGIA GABONENSIS SEED BUTTER; DISTEARDIMONIUM HECTORITE; ALUMINUM OXIDE; POLYGLYCERYL-4 ISOSTEARATE; SILICON DIOXIDE; HYDROGENATED COCO-GLYCERIDES; HEXYL LAURATE; CAPRYLYL GLYCOL; CHLORPHENESIN; LAUROYL LYSINE; PROPYLENE CARBONATE; METHICONE (20 CST); PENTAERYTHRITOL TETRAKIS(3-(3,5-DI-TERT-BUTYL-4-HYDROXYPHENYL)PROPIONATE); SEDUM ROSEUM ROOT; CARNOSINE; TRIETHOXYCAPRYLYLSILANE; ALANYL GLUTAMINE; FERRIC OXIDE YELLOW; FERRIC OXIDE RED; FERROSOFERRIC OXIDE

L'BEL MOUSSE MATIFFIANT MATTE FINISH MOUSSE FOUNDATION SPF 15

Drug Facts

ACTIVE INGREDIENT

Active Ingredients | Purpose
OCTINOXATE 6.5% | Sunscreen
TITANIUM DIOXIDE 2.44% | Sunscreen
ZINC OXIDE 1.57% | Sunscreen

Uses

- Helps prevent sunburn.

Warnings

- Skin Cancer / Skin Aging Alert: Spending time in the sun increases your risk of skin cancer and early skin aging. This product has been shown only to help prevent sunburn, not skin cancer or early skin aging.

- For external use only.

- Do not use on damaged or broken skin.

- When using this product keep out of eyes. Rinse with water to remove.

- Stop use and ask a doctor if rash occurs.

- Keep out of reach of children. If swallowed, get medical help or contact a Poison Control Center right away.

Directions

- Apply liberally and evenly 15 minutes before sun exposure.
- Reapply at least every 2 hours
- Use a water resistant sunscreen if swimming or sweating.
- Children under 6 months of age: Ask a doctor

Other information

- Protect the product in this container from excessive heat and direct sun.

Inactive ingredients

CYCLOPENTASILOXANE, MICA, DIMETHICONE CROSSPOLYMER, DIMETHICONE/VINYL DIMETHICONE CROSSPOLYMER, TRIMETHYLSILOXYSILICATE, CYCLOHEXASILOXANE, BIS-HYDROXYETHOXYPROPYL DIMETHICONE, OCTYLDODECANOL, PHENOXYETHANOL, BORON NITRIDE, IRVINGIA GABONENSIS KERNEL BUTTER, DISTEARDIMONIUM HECTORITE, ALUMINA, CETYL PEG/PPG-10/1 DIMETHICONE, POLYGLYCERYL-4 ISOSTEARATE, SILICA, HYDROGENATED COCO-GLYCERIDES, HEXYL LAURATE, DIMETHICONOL, CAPRYLYL GLYCOL, TOCOPHERYL ACETATE, CHLORPHENESIN, LAUROYL LYSINE, PROPYLENE CARBONATE, METHICONE, PENTAERYTHRITYL TETRA-DI-T-BUTYL HYDROXYHYDROCINNAMATE, RHODIOLA ROSEA ROOT EXTRACT, CARNOSINE, TRIETHOXYCAPRYLYLSILANE, ALANYL GLUTAMINE.

MAY CONTAIN:

TITANIUM DIOXIDE (CI 77891), IRON OXIDES (CI 77492), IRON OXIDES (CI 77491), IRON OXIDES (CI 77499).

Dist. by
Ventura Corp, Ltd., San Juan, Puerto Rico
00926

PRINCIPAL DISPLAY PANEL - 30 g Tube Box - Claire 1/Beige

L'BEL
MOUSSE
MATIFFIANT

Matte finish mousse
foundation SPF 15

Net wt. 1 oz. e (30 g)

PRINCIPAL DISPLAY PANEL - 30 g Tube Box - Claire 2/ Beige

L'BEL
MOUSSE
MATIFFIANT

Matte finish mousse
foundation SPF 15

Net wt. 1 oz. e (30 g)

PRINCIPAL DISPLAY PANEL - 30 g Tube Box - Claire 3/ Beige

L'BEL
MOUSSE
MATIFFIANT

Matte finish mousse
foundation SPF 15

Net wt. 1 oz. e (30 g)

PRINCIPAL DISPLAY PANEL - 30 g Tube Box - Claire 4/ Beige

L'BEL
MOUSSE
MATIFFIANT

Matte finish mousse
foundation SPF 15

Net wt. 1 oz. e (30 g)

PRINCIPAL DISPLAY PANEL - 30 g Tube Box - Medium 5/ Beige

L'BEL
MOUSSE
MATIFFIANT

Matte finish mousse
foundation SPF 15

Net wt. 1 oz. e (30 g)

PRINCIPAL DISPLAY PANEL - 30 g Tube Box - Medium 6/ Beige

L'BEL
MOUSSE
MATIFFIANT

Matte finish mousse
foundation SPF 15

Net wt. 1 oz. e (30 g)

PRINCIPAL DISPLAY PANEL - 30 g Tube Box - Medium 7/ Beige

L'BEL
MOUSSE
MATIFFIANT

Matte finish mousse
foundation SPF 15

Net wt. 1 oz. e (30 g)

PRINCIPAL DISPLAY PANEL - 30 g Tube Box - Obscure 8/ Beige

L'BEL
MOUSSE
MATIFFIANT

Matte finish mousse
foundation SPF 15

Net wt. 1 oz. e (30 g)

PRINCIPAL DISPLAY PANEL - 30 g Tube Box - Obscure 9/ Beige

L'BEL
MOUSSE
MATIFFIANT

Matte finish mousse
foundation SPF 15

Net wt. 1 oz. e (30 g)